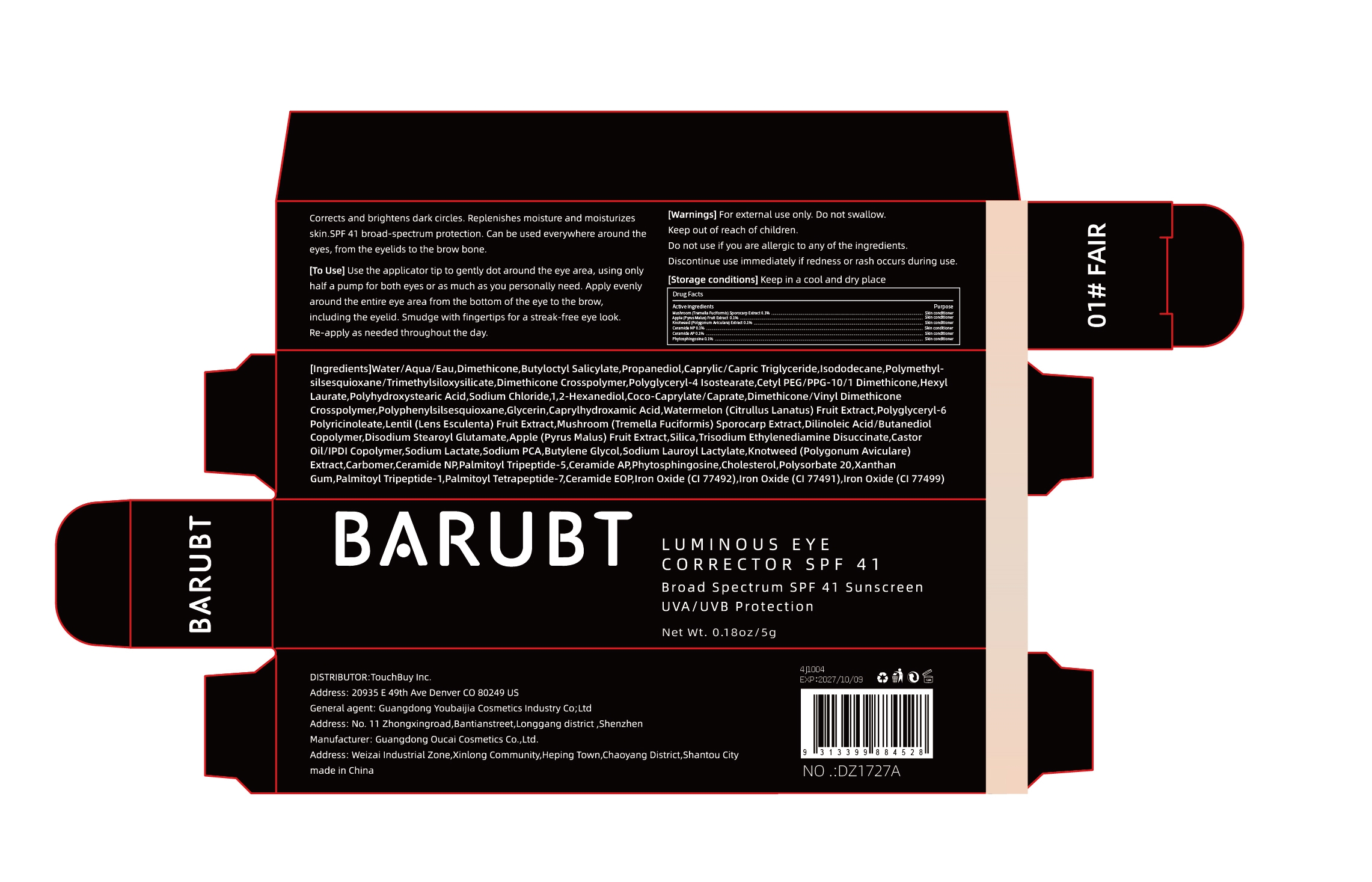 DRUG LABEL: BARUBT LUMINOUS EYE CORRECTOR SPF 41
NDC: 84712-037 | Form: CREAM
Manufacturer: Guangdong Youbaijia Cosmetic Industry Co., Ltd
Category: otc | Type: HUMAN OTC DRUG LABEL
Date: 20241127

ACTIVE INGREDIENTS: CERAMIDE NP 0.05 g/5 g; PHYTOSPHINGOSINE 0.05 g/5 g; PYRUS MALUS (APPLE) FRUIT 0.05 g/5 g; POLYGONUM AVICULARE WHOLE 0.05 g/5 g; CERAMIDE AP 0.05 g/5 g; TREMELLA FUCIFORMIS WHOLE 0.005 g/5 g
INACTIVE INGREDIENTS: PROPANEDIOL 0.2 g/5 g

ACTIVE INGREDIENT

Mushroom (Tremella Fuciformis) Sporocarp Extract 0.1%
Apple (Pyrus Malus) Fruit Extract 0.1%
Knotweed (Polygonum Aviculare) Extract 0.1%
Ceramide NP 0.1%
Ceramide AP 0.1%
Phytosphingosine 0.1%

INACTIVE INGREDIENT

Water/Aqua/Eau
Dimethicone
Butyloctyl Salicylate
Propanediol
Caprylic/Capric Triglyceride
Isododecane
Polymethylsilsesquioxane/Trimethylsiloxysilicate
Dimethicone Crosspolymer
Polyglyceryl-4 Isostearate
Cetyl PEG/PPG-10/1 Dimethicone
Hexyl Laurate
Polyhydroxystearic Acid
Sodium Chloride
1
2-Hexanediol
Coco-Caprylate/Caprate
Dimethicone/Vinyl Dimethicone Crosspolymer
Polyphenylsilsesquioxane
Glycerin
Caprylhydroxamic Acid
Watermelon (Citrullus Lanatus) Fruit Extract
Polyglyceryl-6 Polyricinoleate
Lentil (Lens Esculenta) Fruit Extract
Dilinoleic Acid/Butanediol Copolymer
Disodium Stearoyl Glutamate
Silica
Trisodium Ethylenediamine Disuccinate
Castor Oil/IPDI Copolymer
Sodium Lactate
Sodium PCA
Butylene Glycol
Sodium Lauroyl Lactylate
Carbomer
Palmitoyl Tripeptide-5
Cholesterol
Polysorbate 20
Xanthan Gum
Palmitoyl Tripeptide-1
Palmitoyl Tetrapeptide-7
Ceramide EOP
Iron Oxide (CI 77492)
Iron Oxide (CI 77491)
Iron Oxide (CI 77499)

DO NOT USE

on damaged or broken skin

Keep away from children. Do not swallow.

PURPOSE

Corrects and brightens dark circles.

QUESTIONS

Contact name: Jessie Peng
Company phone number: +1 818 579 7288
Company e-mail: jessie@registeragentllc.com

STOP USE

lf skin becomes red or irritated, discontinue use immediately and wash with water.

WHEN USING

keep out of eyes. Rinse with water to remove.

WARNINGS

For external use only.

INDICATIONS AND USAGE

Corrects and brightens dark circles. Replenishes moisture and moisturizes skin.SPF 41 broad-spectrum protection. Can be used everywhere around the eyes, from the eyelids to the brow bone.

DOSAGE AND ADMINISTRATION

Use the applicator tip to gently dot around the eye area, using only half a pump for both eyes or as much as you personally need. Apply evenly around the entire eye area from the bottom of the eye to the brow,including the eyelid, Smudge with fingertips for a streak-free eye look.Re-apply as needed throughout the day.

STORAGE AND HANDLING

Keep away from light and in a dry place.